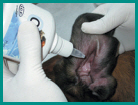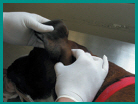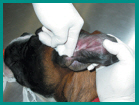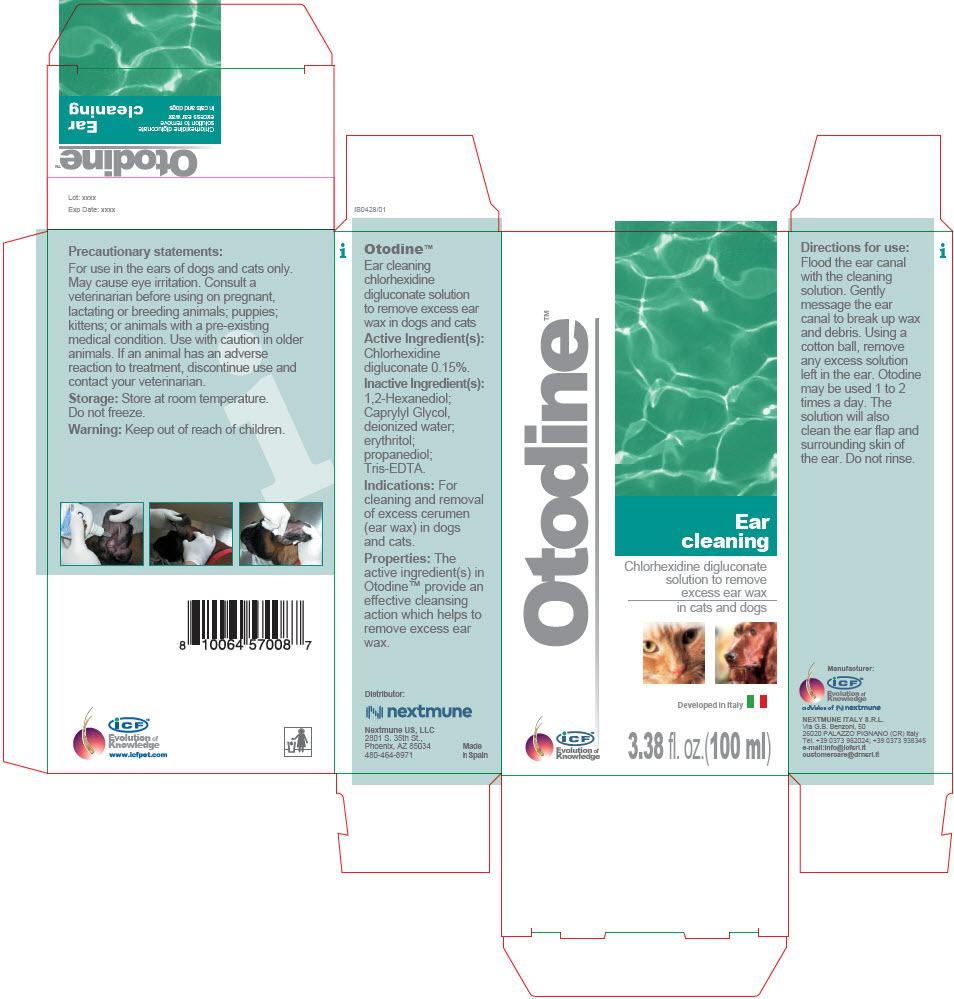 DRUG LABEL: Otodine
NDC: 86127-009 | Form: SOLUTION
Manufacturer: Nextmune AB
Category: animal | Type: OTC ANIMAL DRUG LABEL
Date: 20220111

ACTIVE INGREDIENTS: CHLORHEXIDINE GLUCONATE 1.5 mg/1 mL
INACTIVE INGREDIENTS: water; erythritol; propanediol; Tromethamine; Edetate Sodium; 1,2-Hexanediol; Caprylyl Glycol

Otodine™

VETERINARY INDICATIONS

Ear cleaning chlorhexidine digluconate solution to remove excess ear wax in dogs and cats

Active Ingredient(s):

Chlorhexidine digluconate 0.15%.

Inactive Ingredient(s):

1,2-Hexanediol; Caprylyl Glycol, deionized water; erythritol; propanediol; Tris-EDTA.

INDICATIONS AND USAGE

Indications: For cleaning and removal of excess cerumen (ear wax) in dogs and cats.

Properties: The active ingredient(s) in Otodine™ provide an effective cleansing action which helps to remove excess ear wax.

Directions for use:

Flood the ear canal with the cleaning solution. Gently message the ear canal to break up wax and debris. Using a cotton ball, remove any excess solution left in the ear. Otodine may be used 1 to 2 times a day. The solution will also clean the ear flap and surrounding skin of the ear. Do not rinse.

Precautionary statements:

For use in the ears of dogs and cats only. May cause eye irritation. Consult a veterinarian before using on pregnant, lactating or breeding animals; puppies; kittens; or animals with a pre-existing medical condition. Use with caution in older animals. If an animal has an adverse reaction to treatment, discontinue use and contact your veterinarian.

Storage: Store at room temperature. Do not freeze.

Warning: Keep out of reach of children.

iCF™
Evolution of
Knowledge
www.icfpet.com

Distributor:

Nextmune US, LLC
2801 S. 35th St.,
Phoenix, AZ 85034
480-464-8971

Made
in Spain

Manufacturer:

iCF™
Evolution of
Knowledge

a division of

NEXTMUNE ITALY S.R.L.
Via G.B. Benzoni, 50
26020 PALAZZO PIGNANO (CR) Italy
Tel. +39 0373 982024; +39 0373 938345
e-mail:info@icfsrl.it
customercare@drnsrl.it

PRINCIPAL DISPLAY PANEL - 100 ml Bottle Carton

Otodine™

Ear
cleaning

Chlorhexidine digluconate
solution to remove
excess ear wax

in cats and dogs

Developed in Italy

iCF™
Evolution of
Knowledge

3.38 fl. oz.(100 ml)